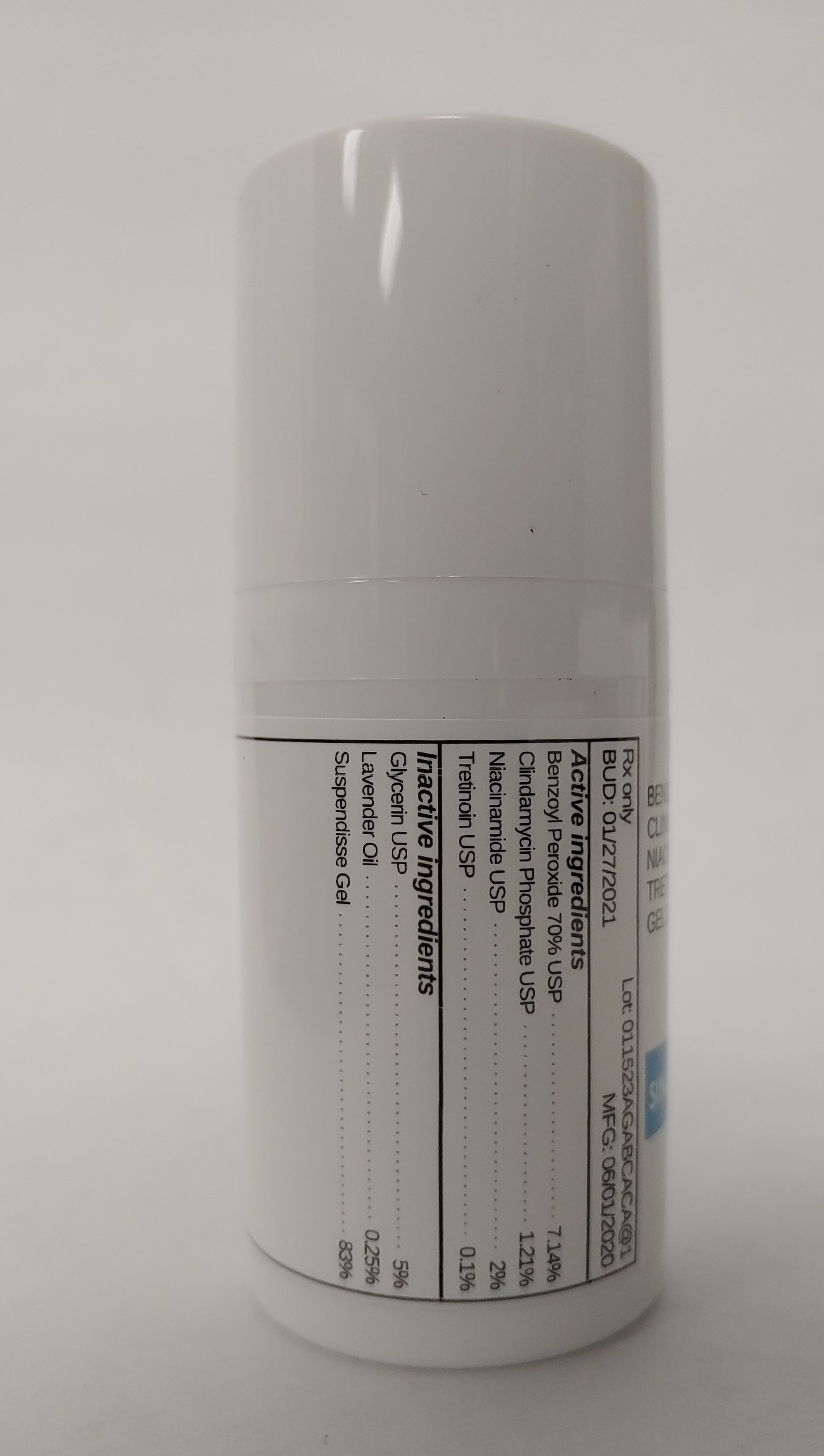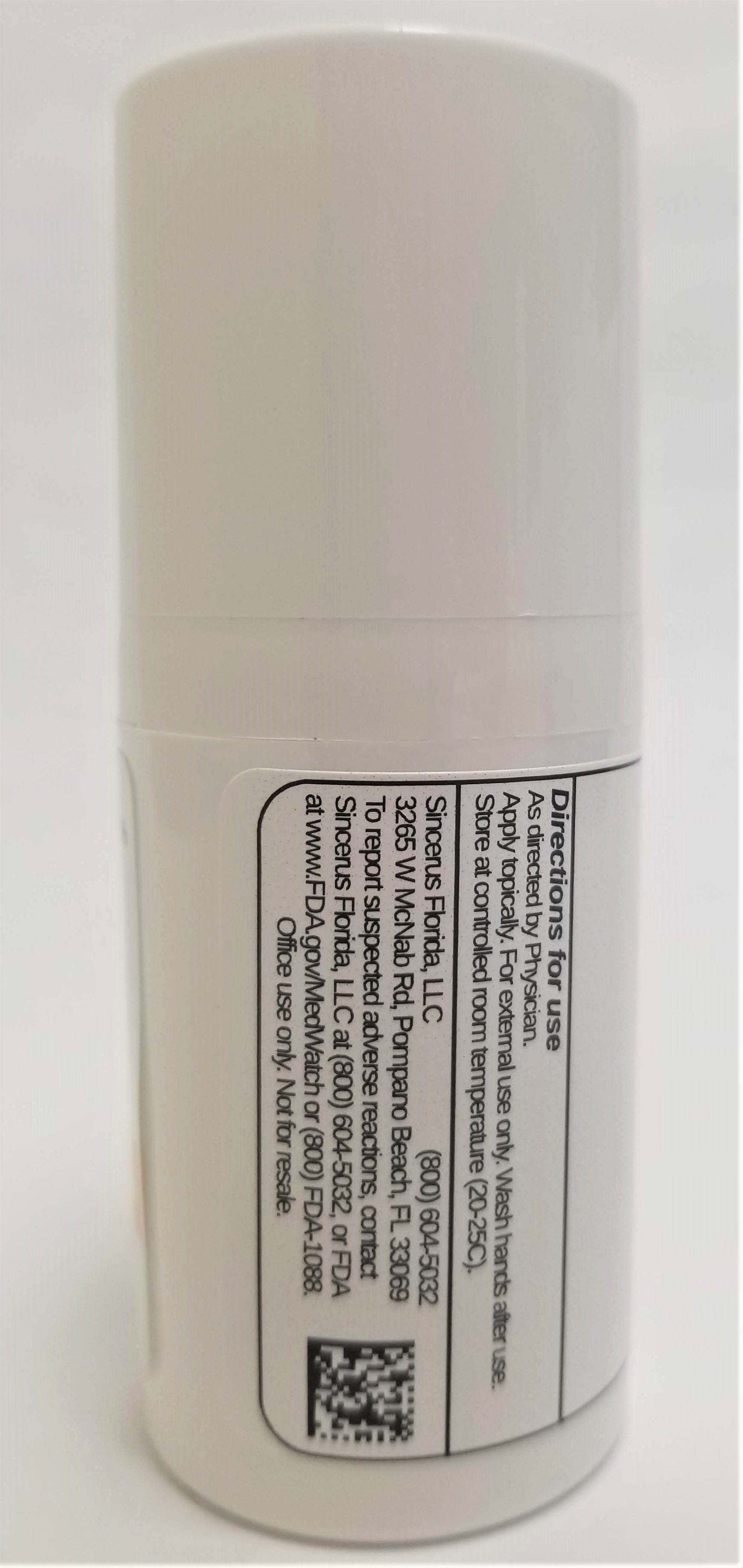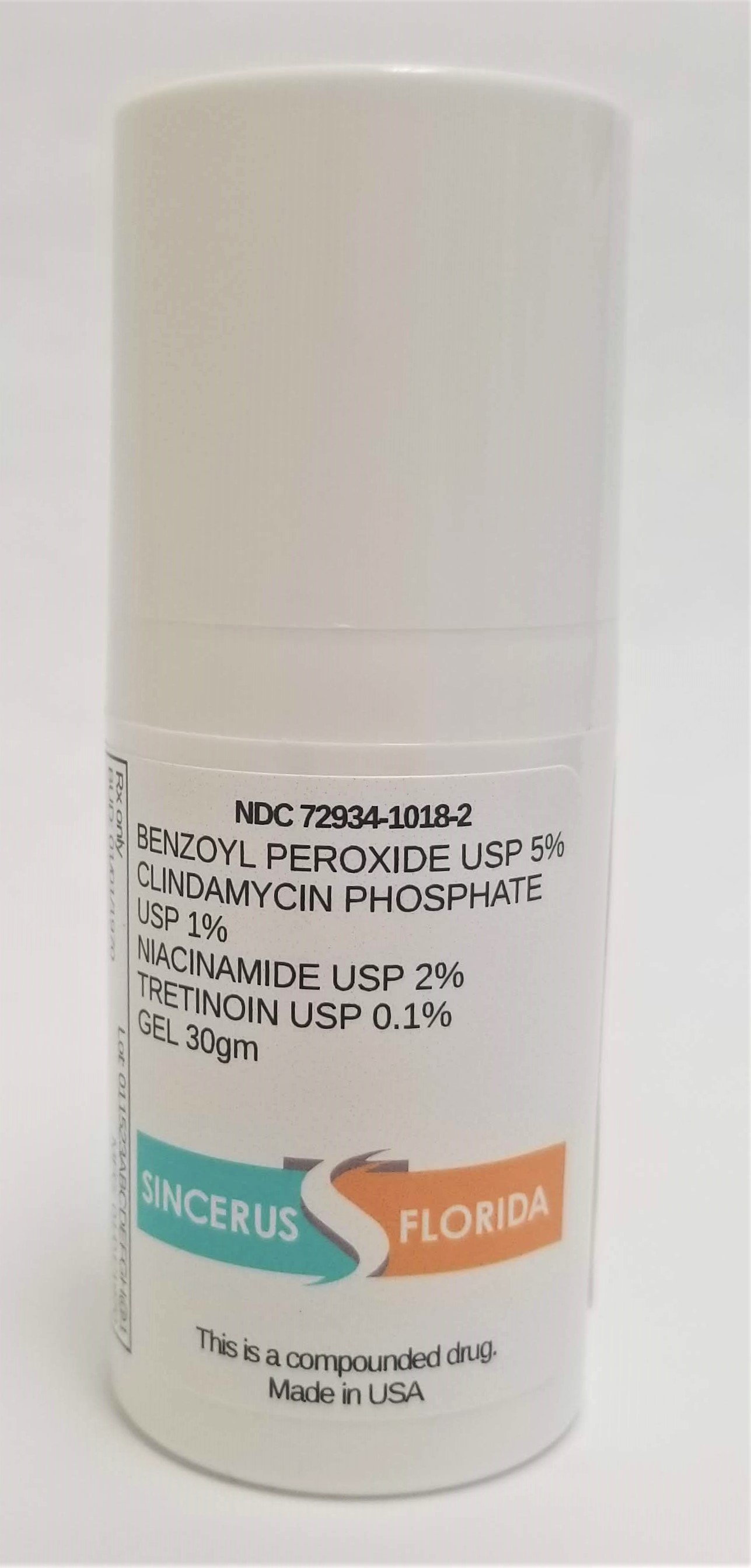 DRUG LABEL: BENZOYL PEROXIDE 5% / CLINDAMYCIN 1% / NIACINAMIDE 2% / TRETINOIN 0.1%
NDC: 72934-1018 | Form: GEL
Manufacturer: Sincerus Florida, LLC
Category: prescription | Type: HUMAN PRESCRIPTION DRUG LABEL
Date: 20200604

ACTIVE INGREDIENTS: BENZOYL PEROXIDE 5 g/100 g; NIACINAMIDE 2 g/100 g; CLINDAMYCIN PHOSPHATE 1 g/100 g; TRETINOIN 0.1 g/100 g

BENZOYL PEROXIDE 5% / CLINDAMYCIN 1% / NIACINAMIDE 2% / TRETINOIN 0.1%